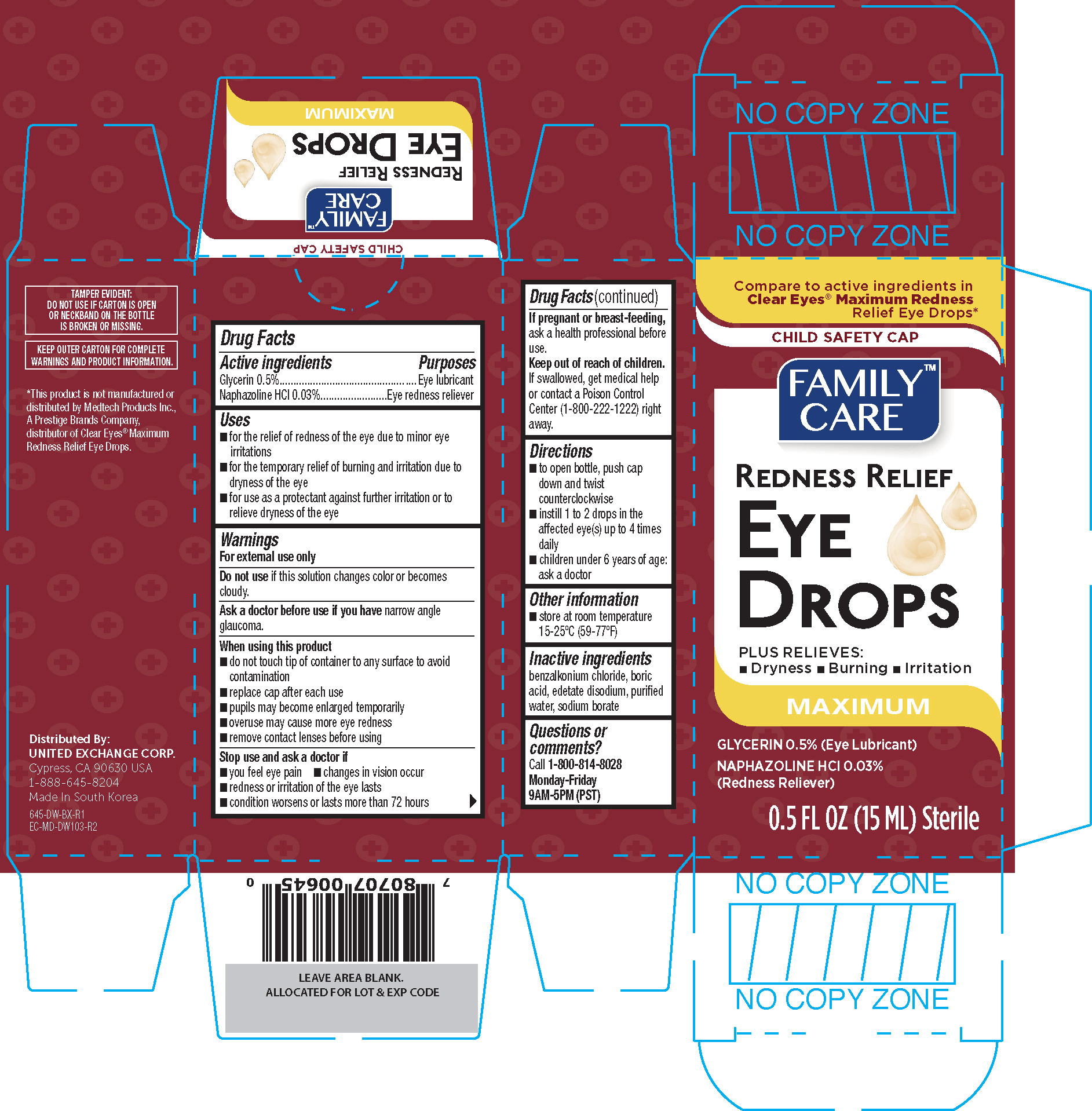 DRUG LABEL: Family Care Redness Relief
NDC: 65923-645 | Form: SOLUTION/ DROPS
Manufacturer: United Exchange Corp.
Category: otc | Type: HUMAN OTC DRUG LABEL
Date: 20251020

ACTIVE INGREDIENTS: NAPHAZOLINE HYDROCHLORIDE 0.3 mg/1 mL; GLYCERIN 5 mg/1 mL
INACTIVE INGREDIENTS: BORIC ACID; EDETATE DISODIUM; WATER; SODIUM BORATE; BENZALKONIUM CHLORIDE

Family Care Maximum Redness Relief Eye Drops 0.5oz 645, 2019 DW

Active ingredients Purposes

Glycerin 0.5%........................................................................Eye lubricant

Naphazoline HCl 0.03............................................................Eye redness reliever

Uses

- for the relief of redness of the eye due to minor eye irritations
- for the temporary relief of burning and irritation due to dryness of the eye
- for use as a protectant against further irritation or to relieve dryness of the eye

Warnings

For external use only

Do not use if this solution changes color or becomes cloudy.

Ask a doctor before use if you have narrow angle glaucoma.

When using this product

- do not touch tip of container to any surface to avoid contamination
- replace cap after each use
- pupils may become enlarged temporarily
- overuse may cause more eye redness
- remove contact lenses before using

Stop use and ask a doctor if

- you feel eye pain
- changes in vision occur
- redness or irritation of the eye lasts
- condition worsens or lasts more than 72 hours

PREGNANCY OR BREAST FEEDING

If pregnant or breast-feeding, ask a health professional before use.

Keep out of reach of children. If swallowed, get medical help or contact a Poison Control Center (1-800-222-1222) right away.

Directions

- to open bottle, push cap down and twist counterclockwise
- instill 1 to 2 drops in the affected eye(s) up to 4 times daily
- children under 6 years of age: ask a doctor

Other information

- store at room temperature 15-25°F (59-77°F)

Inactive ingredients

benzalkonium chloride, boric acid, edetate disodium, purified water, sodium borate

DOSAGE AND ADMINISTRATION

Distributed by:

United Exchange Corp.

Cypress, CA 90630 USA

Made in South Korea